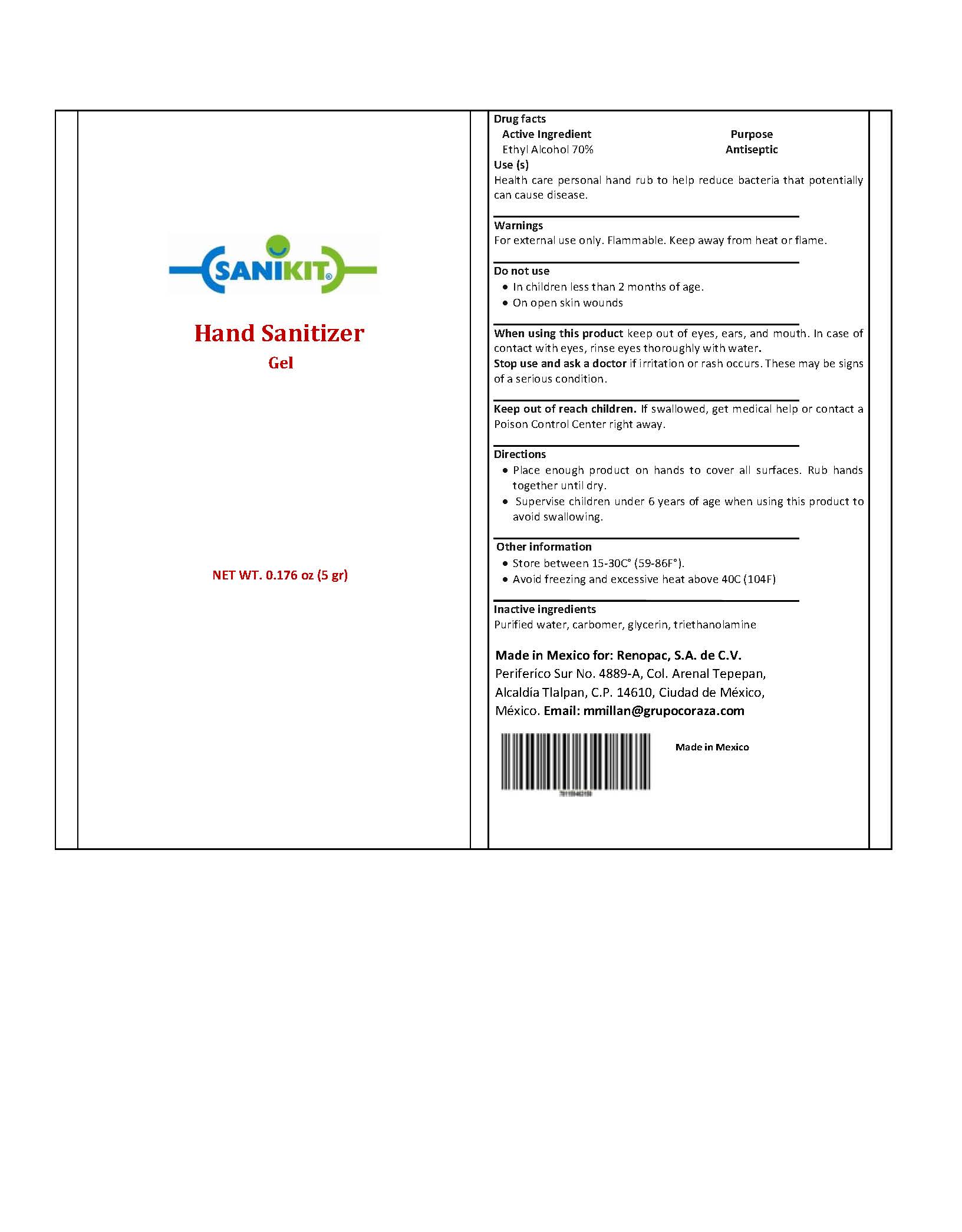 DRUG LABEL: Sanikit
NDC: 79067-004 | Form: GEL
Manufacturer: Renopac, S.A. de C.V.
Category: otc | Type: HUMAN OTC DRUG LABEL
Date: 20230712

ACTIVE INGREDIENTS: ALCOHOL 70 mL/100 mL
INACTIVE INGREDIENTS: CARBOMER HOMOPOLYMER, UNSPECIFIED TYPE; GLYCERIN; TROLAMINE; WATER

ACTIVE INGREDIENT - OTC - ACTIVE INGREDIENT SECTION

Ethyl Alcohol 70% (w/w)

PURPOSE - OTC - PURPOSE SECTION

Antiseptic

USES - INDICATIONS AND USAGE SECTION

Health care personal hand rub to help reduce bacteria that potentially can cause disease

WARNINGS - WARNINGS SECTIONS

For external use only.

Flammable.

Kepp away from heat or flame.

WHEN USING THIS PRODUCT - WHEN USING SECTION

Keep out of eyes, ears, and mouth.

In case of contact with eyes, rinse eyes thoroughly with water.

STOP USE AND ASK A DOCTOR - STOP USE SECTION

If irritation or rash occur. These may be signs of a serious condition.

KEEP OUT OF REACH OF CHILDREN - KEEP OUT OF REACH OF CHILDREN SECTION

If swallowed, get medical help por contact a Poison Control right away.

DIRECTIONS - DOSAGE AND ADMINISTRATION SECTION

Place enough product on hands to cover all surfaces. Rub hands together until dry.

Supervise children under 6 years of age when using this product to avoid swallowing.

OTHER INFORMATION - STORAGE AND HANDLING SECTION

Store between 15-30ºC (59-86ºF)

Avoid freezing and excessive heat above 40ºC (104ºF)

INACTIVE INGREDIENTS - INACTIVE INGREDIENT SECTION

Purified water, carbomer, glycerin, triethanolamine.

PACKAGE LABEL. PRINCIPAL DISPLAY PANEL

SANIKIT 5g NDC - 79067-004-01